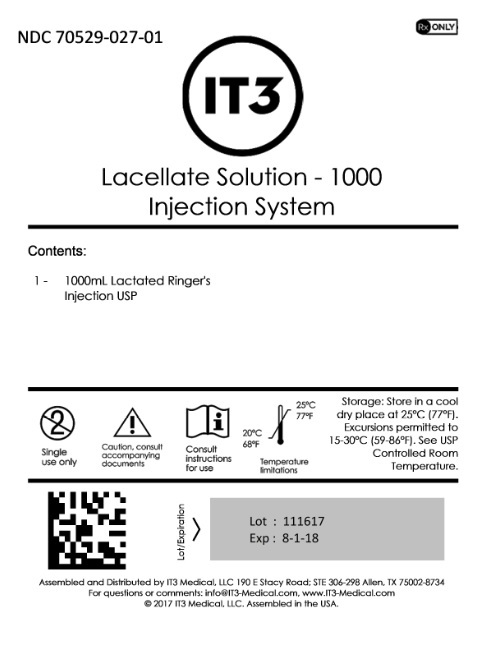 DRUG LABEL: Lacellate Solution - 1000
NDC: 70529-027 | Form: INJECTION, SOLUTION
Manufacturer: IT3 Medical LLC
Category: prescription | Type: HUMAN PRESCRIPTION DRUG LABEL
Date: 20220223

ACTIVE INGREDIENTS: SODIUM CHLORIDE 600 mg/100 mL; SODIUM LACTATE 310 mg/100 mL; POTASSIUM CHLORIDE 30 mg/100 mL; CALCIUM CHLORIDE 20 mg/100 mL
INACTIVE INGREDIENTS: WATER

Lacellate Solution - 1000

DESCRIPTION

Lactated Ringer’s Injection, USP is a sterile, nonpyrogenic solution for fluid and electrolyte replenishment in single dose containers for intravenous administration. It contains no antimicrobial agents. Composition, osmolarity, pH, ionic concentration and caloric content are shown in Table 1.

Table 1
 |  | Composition (g/L) |  |  |  |  |  | Ionic Composition (mEq/L)
 | Size (mL) | Sodium Chloride, USP, (NaCl) | Sodium Lactate, (C3H5NaO3) | Potassium Chloride, USP, (KCl) | Calcium Chloride, USP (CaCl2·2H2O) | Osmolarity (mOsmol/L) (calc) | pH | Sodium | Potassium | Calcium | Chloride | Lactate | Caloric Content (kcal/L)
Lactated Ringer’s Injection, USP | 250; 500; 1000 | 6 | 3.1 | 0.3 | 0.2 | 273 | 6.5 (6.0 to 7.5) | 130 | 4 | 2.7 | 109 | 28 | 9

The VIAFLEX plastic container is fabricated from a specially formulated polyvinyl chloride (PL 146 Plastic). The amount of water that can permeate from inside the container into the overwrap is insufficient to affect the solution significantly. Solutions in contact with the plastic container can leach out certain of its chemical components in very small amounts within the expiration period, e.g., di-2-ethylhexyl phthalate (DEHP), up to 5 parts per million. However, the safety of the plastic has been confirmed in tests in animals according to USP biological tests for plastic containers as well as by tissue culture toxicity studies.

CLINICAL PHARMACOLOGY

Lactated Ringer’s Injection, USP has value as a source of water and electrolytes. It is capable of inducing diuresis depending on the clinical condition of the patient.

Lactated Ringer’s Injection, USP produces a metabolic alkalinizing effect. Lactate ions are metabolized ultimately to carbon dioxide and water, which requires the consumption of hydrogen cations.

INDICATIONS AND USAGE

Lactated Ringer’s Injection, USP is indicated as a source of water and electrolytes or as an alkalinizing agent.

CONTRAINDICATIONS

As for other calcium-containing infusion solutions, concomitant administration of ceftriaxone and Lactated Ringer’s Injection, USP is contraindicated in newborns (≤ 28 days of age), even if separate infusion lines are used (risk of fatal ceftriaxone-calcium salt precipitation in the neonate’s bloodstream).

In patients older than 28 days (including adults), ceftriaxone must not be administered simultaneously with intravenous calcium-containing solutions, including Lactated Ringer’s Injection, USP, through the same infusion line (e.g., via Y-connector).
If the same infusion line is used for sequential administration, the line must be thoroughly flushed between infusions with a compatible fluid.

Lactated Ringer’s Injection, USP is contraindicated in patients with a known hypersensitivity to sodium lactate.

WARNINGS

Although Lactated Ringer’s Injection, USP has a potassium concentration similar to the concentration in plasma, it is insufficient to produce a useful effect in case of severe potassium deficiency; therefore, it should not be used for this purpose.

Lactated Ringer’s Injection, USP is not for use for the treatment of lactic acidosis or severe metabolic acidosis.

Lactated Ringer’s Injection, USP should not be administered simultaneously with citrate anticoagulated/preserved blood through the same administration set because of the likelihood of coagulation.

The infusion must be stopped immediately if any signs or symptoms of a suspected hypersensitivity reaction develop. Appropriate therapeutic countermeasures must be instituted as clinically indicated. Hypersensitivity reactions are reported more frequently during pregnancy.

Depending on the volume and the rate of infusion, the intravenous administration of Lactated Ringer’s Injection, USP can cause fluid and/or solute overloading resulting in dilution of serum electrolyte concentrations, overhydration, congested states, pulmonary edema or acid-base imbalance. The risk of dilutional states is inversely proportional to the electrolyte concentrations of the injections. The risk of solute overload causing congested states with peripheral and pulmonary edema is directly proportional to the electrolyte concentrations of the injections.

Clinical evaluation and periodic laboratory determinations may be necessary to monitor changes in fluid balance, electrolyte concentrations, and acid base balance during prolonged parenteral therapy or whenever the condition of the patient or the rate of administration warrants such evaluation.

Lactated Ringer’s Injection, USP should be administered with particular caution, if at all, to patients with hyperkalemia or conditions predisposing to hyperkalemia (such as severe renal impairment or adrenocortical insufficiency, acute dehydration, or extensive tissue injury or burns) and in patients with cardiac disease.

Lactated Ringer’s Injection, USP should be administered with particular caution, if at all, to patients with alkalosis or at risk for alkalosis. Because lactate is metabolized to bicarbonate, administration may result in, or worsen, metabolic alkalosis.

Lactated Ringer’s Injection, USP should be administered with particular caution, if at all, to patients with severe renal impairment, hypervolemia, overhydration, or conditions that may cause sodium and/or potassium retention, fluid overload, or edema.

PRECAUTIONS

Do not connect flexible plastic containers in series in order to avoid air embolism due to possible residual air contained in the primary container.

Pressurizing intravenous solutions contained in flexible plastic containers to increase flow rates can result in air embolism if the residual air in the container is not fully evacuated prior to administration.

Use of a vented intravenous administration set with the vent in the open position could result in air embolism. Vented intravenous administration sets with the vent in the open position should not be used with flexible plastic containers.

Lactated Ringer’s Injection, USP should be administered with particular caution, if at all, to patients with conditions associated with increased lactate levels or impaired lactate utilization, such as severe hepatic insufficiency.

Hyperlactatemia can develop in patients with severe hepatic insufficiency, since lactate metabolism may be impaired. In addition Lactated Ringer’s Injection, USP may not produce its alkalinizing action in patients with severe hepatic insufficiency, since lactate metabolism may be impaired.

Solutions containing calcium salts should be used with caution in patients with hypercalcemia or conditions predisposing to hypercalemia, such as patients with severe renal impairment and granulomatous diseases associated with increased calcitriol synthesis such as sarcoidosis, calcium renal calculi or history of such calculi.

Lactate is a substrate for gluconeogenesis. This should be taken into account when Lactated Ringer’s Injection, USP is used in patients with type 2 diabetes.

Pediatric Use

Safety and effectiveness of Lactated Ringer’s Injection, USP in pediatric patients have not been established by adequate and well controlled trials, however, the use of electrolyte solutions in the pediatric population is referenced in the medical literature. The warnings, precautions and adverse reactions identified in the label copy should be observed in the pediatric population.

Lactate-containing solutions should be administered with particular caution to neonates and infants less than 6 months of age.

Geriatric Use

Clinical studies of Lactated Ringer’s Injection, USP did not include sufficient numbers of subjects aged 65 and over to determine whether they respond differently from younger subjects. Other reported clinical experience has not identified differences in responses between the elderly and younger patients. In general, dose selection for an elderly patient should be cautious, usually starting at the low end of the dosing range, reflecting the greater frequency of decreased hepatic, renal, or cardiac function, and of concomitant disease or other drug therapy.

Drug Interactions

Ceftriaxone – see CONTRAINDICATIONS

Caution is advised when administering Lactated Ringer’s Injection, USP to patients treated with drugs that may increase the risk of sodium and fluid retention, such as corticosteroids.

Caution is advised when administering Lactated Ringer’s Injection, USP to patients treated with drugs for which renal elimination is pH dependent. Due to the alkalinizing action of lactate (formation of bicarbonate), Lactated Ringer’s Injection, USP may interfere with the elimination of such drugs.

1. Renal clearance of acidic drugs such as salicylates and barbiturates may be increased.
2. Renal clearance of alkaline drugs, such as sympathomimetics (e.g., ephedrine, pseudoephedrine) and dextroamphetamine (dexamphetamine) sulfate, may be decreased.

Renal clearance of lithium may also be increased. Caution is advised when administering Lactated Ringer’s Injection, USP to patients treated with lithium.

Because of its potassium content, Lactated Ringer’s Injection, USP should be administered with caution in patients treated with agents or products that can cause hyperkalemia or increase risk of hyperkalemia, such as potassium sparing diuretics (amiloride, spironolactone, triamterene), with ACE inhibitors, angiotensin II receptor antagonists, or the immunosuppressants tacrolimus and cyclosporine.

Caution is advised when administering Lactated Ringer’s Injection, USP to patients treated with thiazide diuretics or vitamin D, as these can increase the risk of hypercalcemia.

Pregnancy

Teratogenic Effects

Animal reproduction studies have not been conducted with Lactated Ringer’s Injection, USP. It is also not known whether Lactated Ringer’s Injection, USP can cause fetal harm when administered to a pregnant woman or can affect reproduction capacity. Lactated Ringer’s Injection, USP should be given to a pregnant woman only if clearly needed.

For Hypersensitivity Reactions During Pregnancy – see WARNINGS

Carcinogenesis, Mutagenesis, Impairment of Fertility

Long-term studies in animals to evaluate carcinogenic potential or studies to evaluate mutagenic potential have not been performed with Lactated Ringer’s Injection, USP. Studies to evaluate the possible impairment of fertility have not been performed.

Labor and Delivery

Studies have not been conducted to evaluate the effects of Lactated Ringer’s Injection, USP on labor and delivery. Caution should be exercised when administering this drug during labor and delivery.

Nursing Mothers

It is not known whether this drug is excreted in human milk. Because many drugs are excreted in human milk, caution should be exercised when Lactated Ringer’s Injection, USP is administered to a nursing mother.

ADVERSE REACTIONS

Post-Marketing Adverse Reactions

The following adverse reactions have been reported in the post-marketing experience, listed by MedDRA System Organ Class (SOC).

Immune System Disorders: Hypersensitivity/infusion reactions, including anaphylactic/anaphylactoid reactions, and the following manifestations: angioedema, chest pain, chest discomfort, decreased heart rate, tachycardia, blood pressure decreased, respiratory distress, bronchospasm, dyspnea, cough, urticaria, rash, pruritus, erythema, flushing, throat irritation, paresthesias, hypoesthesia oral, dysgeusia, nausea, anxiety, pyrexia, headache

Metabolism and Nutrition Disorders: Hyperkalemia

General Disorders and Administration Site Conditions:
Infusion site reactions, including phlebitis, infusion site inflammation, infusion site swelling, infusion site rash, infusion site pruritus, infusion site erythema, infusion site pain, infusion site burning

Class Reactions

Hypersensitivity reactions, including, laryngeal edema and sneezing

Hypervolemia

Infusion site reactions, including Infection at the site of injection, extravasation, and infusion site anesthesia (numbness)

Overdose

An excessive volume or too high a rate of administration of Lactated Ringer’s Injection, USP may lead to fluid and sodium overload with a risk of edema (peripheral and/or pulmonary), particularly when renal sodium excretion is impaired.

Excessive administration of lactate may lead to metabolic alkalosis. Metabolic alkalosis may be accompanied by hypokalemia.

Excessive administration of potassium may lead to the development of hyperkalemia, especially in patients with severe renal impairment.

Excessive administration of calcium salts may lead to hypercalcemia.

When assessing an overdose, any additives in the solution must also be considered.

The effects of an overdose may require immediate medical attention and treatment.

DOSAGE AND ADMINISTRATION

As directed by a physician. Dosage, rate and duration of administration are to be individualized and dependent upon the indication for use, the patient’s age, weight, concomitant treatment and clinical condition of the patient as well as laboratory determinations.

All injections in VIAFLEX plastic containers are intended for intravenous administration using sterile and nonpyrogenic equipment.

After opening the container, the contents should be used immediately and should not be stored for a subsequent infusion. Do not reconnect any partially used containers.

Parenteral drug products should be inspected visually for particulate matter and discoloration prior to administration whenever solution and container permit. Do not administer unless the solution is clear and seal is intact.

When making additions to Lactated Ringer’s Injection, USP, aseptic technique must be used. Mix the solution thoroughly when additives have been introduced. Do not store solutions containing additives.

Additives may be incompatible with Lactated Ringer’s Injection, USP. As with all parenteral solutions, compatibility of the additives with the solution must be assessed before addition, by checking for a possible color change and/or the appearance of precipitates, insoluble complexes, or crystals. Before adding a substance or medication, verify that it is soluble and/or stable in water and that the pH range of Lactated Ringer’s Injection, USP is appropriate.

The instructions for use of the medication to be added and other relevant literature must be consulted. Additives known or determined to be incompatible should not be used.

HOW SUPPLIED

Lactated Ringer’s Injection, USP in VIAFLEX plastic container is available as follows:

Code | Size (mL) | NDC
2B2324 | 1000 | 70529-027-01

Exposure of pharmaceutical products to heat should be minimized. Avoid excessive heat. It is recommended the product be stored at room temperature (25°C); brief exposure up to 40°C does not adversely affect the product.

DIRECTIONS FOR USE OF VIAFLEX PLASTIC CONTAINER

For Information on Risk of Air Embolism – see PRECAUTIONS

To Open

Tear overwrap down side at slit and remove solution container. Visually inspect the container. If the outlet port protector is damaged, detached, or not present, discard container as solution path sterility may be impaired. Some opacity of the plastic due to moisture absorption during the sterilization process may be observed. This is normal and does not affect the solution quality or safety. The opacity will diminish gradually. Check for minute leaks by squeezing inner bag firmly. If leaks are found, discard solution as sterility may be impaired. If supplemental medication is desired, follow directions below.

Preparation for Administration

1. Suspend container from eyelet support.
2. Remove protector from outlet port at bottom of container.
3. Attach administration set. Refer to complete directions accompanying set.

To add medication before solution administration

1. Prepare medication site.
2. Using syringe with 19 to 22 gauge needle, puncture medication port and inject.
3. Mix solution and medication thoroughly. For high density medication such as potassium chloride, squeeze ports while ports are upright and mix thoroughly.

To add medication during solution administration

1. Close clamp on the set.
2. Prepare medication site.
3. Using syringe with 19 to 22 gauge needle, puncture resealable medication port and inject.
4. Remove container from IV pole and/or turn to an upright position.
5. Evacuate both ports by squeezing them while container is in the upright position.
6. Mix solution and medication thoroughly.
7. Return container to in use position and continue administration.

07-19-00-0202

Rev. January 2018

Assembled and Distributed by IT3 Medical, LLC 190 E Stacy Road; STE 306-298, Allen, TX 75002-8734
For questions or comments: info@IT3-Medical.com, www.IT3-Medical.com